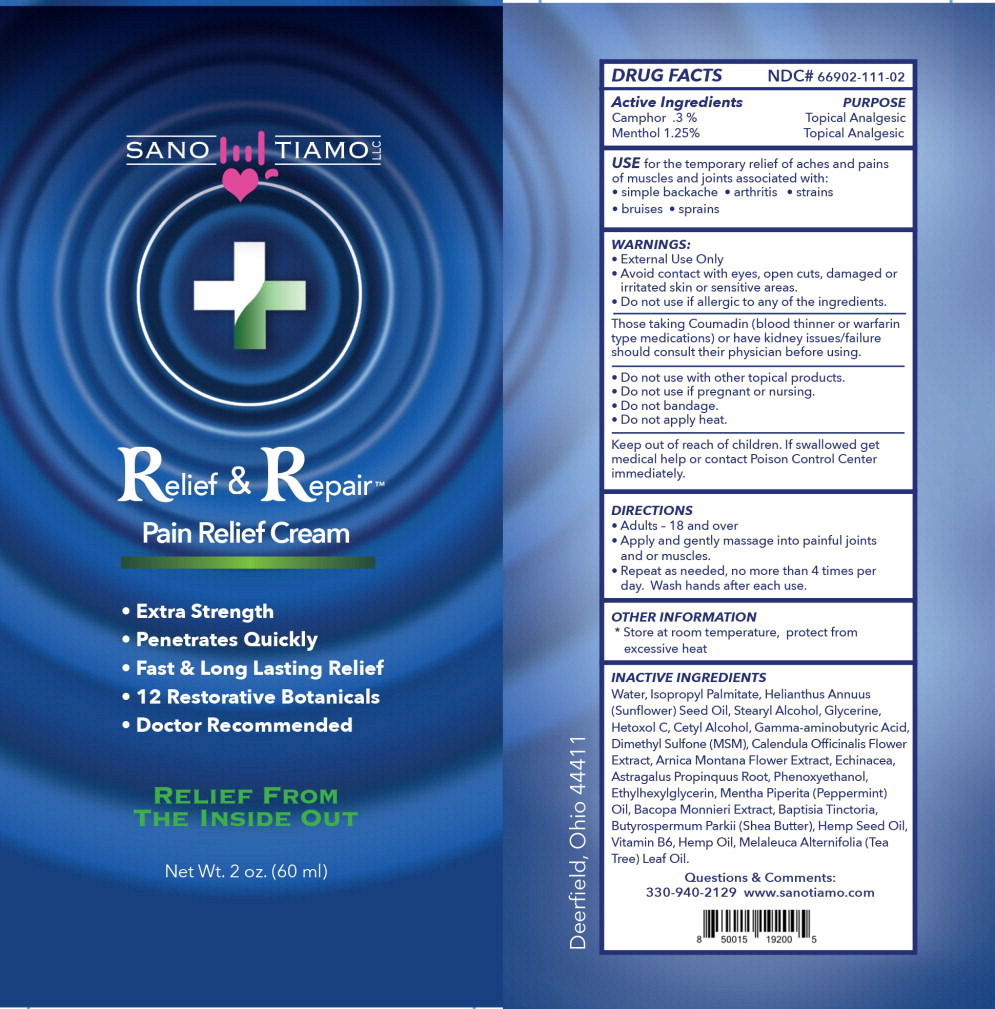 DRUG LABEL: SANO TI AMO RELIEF AND REPAIR PAIN RELIEF
NDC: 80216-111 | Form: CREAM
Manufacturer: Sano Ti Amo, LLC
Category: otc | Type: HUMAN OTC DRUG LABEL
Date: 20250311

ACTIVE INGREDIENTS: MENTHOL, UNSPECIFIED FORM 13.4 mg/1 mL; CAMPHOR (SYNTHETIC) 3.0 mg/1 mL
INACTIVE INGREDIENTS: WATER; ISOPROPYL PALMITATE; SUNFLOWER OIL; STEARYL ALCOHOL; GLYCERIN; PPG-30 CETYL ETHER; CETYL ALCOHOL; .GAMMA.-AMINOBUTYRIC ACID; DIMETHYL SULFONE; ECHINACEA PURPUREA FLOWERING TOP; ECHINACEA PURPUREA ROOT; ECHINACEA ANGUSTIFOLIA ROOT; ASTRAGALUS PROPINQUUS ROOT; BAPTISIA TINCTORIA; BACOPA MONNIERI WHOLE; CALENDULA OFFICINALIS FLOWER; ARNICA MONTANA; PHENOXYETHANOL; ETHYLHEXYLGLYCERIN; PEPPERMINT OIL; SHEA BUTTER; CANNABIS SATIVA SEED OIL; PYRIDOXINE; CANNABIS SATIVA WHOLE; TEA TREE OIL

DRUG FACTS

NDC# 80216-111-02

Active Ingredients

Camphor .3 %

Menthol 1.25%

PURPOSE

Topical Analgesic

Topical Analgesic

INDICATIONS AND USAGE

USE for the temporary relief of aches and pains of muscles and joints associated with:

- simple backache
- arthritis
- strains
- bruises
- sprains

WARNINGS:

- External Use Only
- Avoid contact with eyes, open cuts, damaged or irritated skin or sensitive areas.
- Do not use if allergic to any of the ingredients.

Those taking Coumadin (blood thinner or warfarin type medications) or have kidney issues/failure should consult their physician before using.

- Do not use with other topical products.
- Do not use if pregnant or nursing.
- Do not bandage.
- Do not apply heat.

Keep out of reach of children. If swallowed get medical help or contact Poison Control Center immediately.

DIRECTIONS

- Adults – 18 and over
- Apply and gently massage into painful joints and or muscles.
- Repeat as needed, no more than 4 times per day. Wash hands after each use.

OTHER INFORMATION

* Store at room temperature, protect from excessive heat

INACTIVE INGREDIENTS

Water, Isopropyl Palmitate, Helianthus Annuus (Sunflower) Seed Oil, Stearyl Alcohol, Glycerine, Hetoxol C, Cetyl Alcohol, Gamma-aminobutyric Acid, Dimethyl Sulfone (MSM), Calendula Officinalis Flower Extract, Arnica Montana Flower Extract, Echinacea, Astragalus Propinquus Root, Phenoxyethanol, Ethylhexylglycerin, Mentha Piperita (Peppermint) Oil, Bacopa Monnieri Extract, Baptisia Tinctoria, Butyrospermum Parkii (Shea Butter), Hemp Seed Oil, Vitamin B6, Hemp Oil, Melaleuca Alternifolia (Tea Tree) Leaf Oil.

Questions & Comments:

330-940-2129
www.sanotiamo.com
Deerfield, Ohio 44411

Principal Display Panel – 2 oz Container Label

SANO TI AMO LLC

Relief & Repair™

Pain Relief Cream

- Extra Strength
- Penetrates Quickly
- Fast & Long Lasting Relief
- 12 Restorative Botanicals
- Doctor Recommended

RELIEF FROM
THE INSIDE OUT

Net Wt. 2 oz. (60 ml)